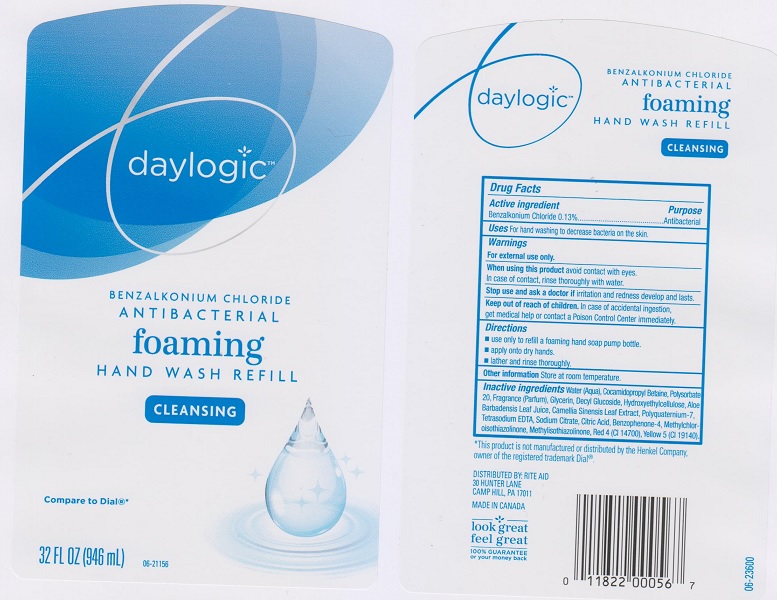 DRUG LABEL: Daylogic Antibacterial Foaming Wash Refill
NDC: 11822-1243 | Form: LIQUID
Manufacturer: Rite Aid Corporation
Category: otc | Type: HUMAN OTC DRUG LABEL
Date: 20170524

ACTIVE INGREDIENTS: BENZALKONIUM CHLORIDE 1.3 mg/1 mL
INACTIVE INGREDIENTS: WATER; COCAMIDOPROPYL BETAINE; POLYSORBATE 20; GLYCERIN; DECYL GLUCOSIDE; POWDERED CELLULOSE; ALOE VERA LEAF; GREEN TEA LEAF; POLYQUATERNIUM-7 (70/30 ACRYLAMIDE/DADMAC; 1600000 MW); EDETATE SODIUM; SODIUM CITRATE; CITRIC ACID MONOHYDRATE; SULISOBENZONE; METHYLCHLOROISOTHIAZOLINONE; METHYLISOTHIAZOLINONE; FD&C RED NO. 4; FD&C YELLOW NO. 5

Drug Facts

Active ingredient

Benzalkonium Chloride 0.13%

Purpose

Antibacterial

Uses

for hand washing to decrease bacteria on the skin.

Warnings

For external use only

When using this product

avoid contact with eyes. In case of contact, rinse thoroughly with water.

Stop use and ask a doctor if

irritation and redness develop and lasts.

Keep out of reach of children.

In case of accidental ingestion, get medical help or contact a Poison Control Center immediately.

Directions

- use only to refill a refoaming hand soap pump bottle
- apply onto dry hands.
- lather and rinse thoroughly

Other information

store at room temperature

Inactive ingredients

Water (Aqua), Cocamidopropyl Betaine, Polysorbate 20, Fragrance (Parfum), Glycerin, Decyl Glucoside, Hydroxyethylcellulose, Aloe Barbadensis Leaf Juice, Camellia Sinensis Leaf Extract, Polyquaternium-7, Tetrasodium EDTA, Sodium Citrate, Citric Acid, Benzophenone-4, Methylchloroisothiazolinone, Methyliosthiazolinone, Red 4 (CI 14700), Yellow 5 (CI 19140).